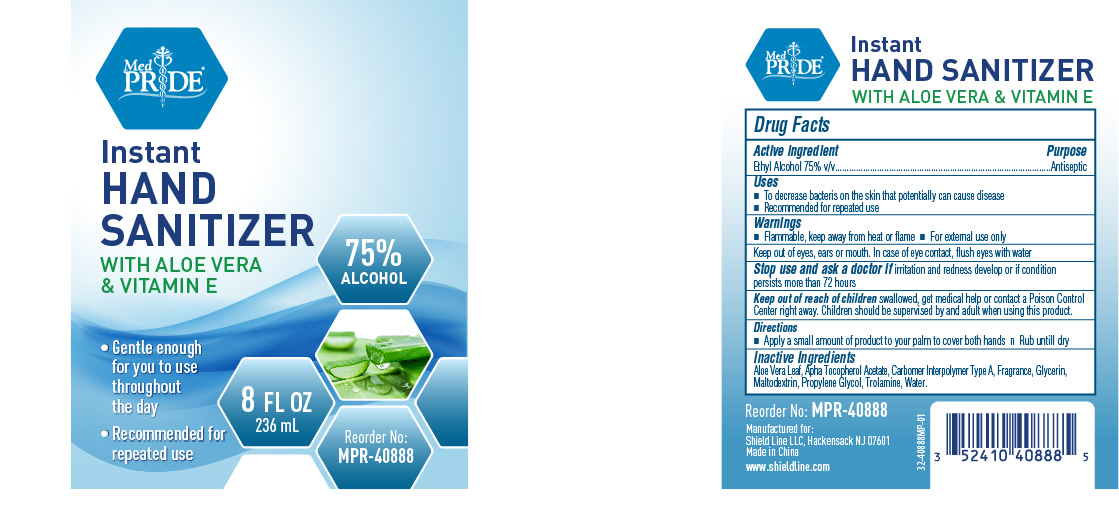 DRUG LABEL: MedPride Instant Sanitizer
NDC: 52410-4088 | Form: GEL
Manufacturer: SHIELD LINE LLC
Category: otc | Type: HUMAN OTC DRUG LABEL
Date: 20251202

ACTIVE INGREDIENTS: ALCOHOL 75 mL/100 mL
INACTIVE INGREDIENTS: ALOE VERA LEAF; ALPHA-TOCOPHEROL; WATER; GLYCERIN; ACRYLATES/C10-30 ALKYL ACRYLATE CROSSPOLYMER (60000 MPA.S); PROPYLENE GLYCOL; AMINOMETHYLPROPANOL; DENATONIUM BENZOATE

MedPride Instant hand Sanitizer

Active Ingredient

Ethyl Alcohol 75% v/v

Purpose

Antiseptic

Keep out of reach of children.

If swallowed, get medical help or contact a Poison Control Center right away. Children should be supervised by an adult when using this product.

Uses

- To decrease bacteria on the skin that potentially can cause disease.
- Recommended for repeated use.

Warnings

- Flammable, keep away from heat or flame
- For external use only

Other Information

Keep out of eyes, ears or mouth. In case of eye contact, flush with water.

May discolor certain fabrics and surfaces.

Stop use and ask a doctor

if irritation and redness develop or if condition persists more than 72 hours.

Directions

- Apply sufficient amount of product to your palm to cover both hands.
- Rub until dry.

Inactive Ingredients

Aloe Vera Lear, Alpha Tocopherol Acetate, Carbomer Interpolymer Type A, Fragrance, Glycerin, Maltodextrin, Propylene Glycol, Trolamine, Water